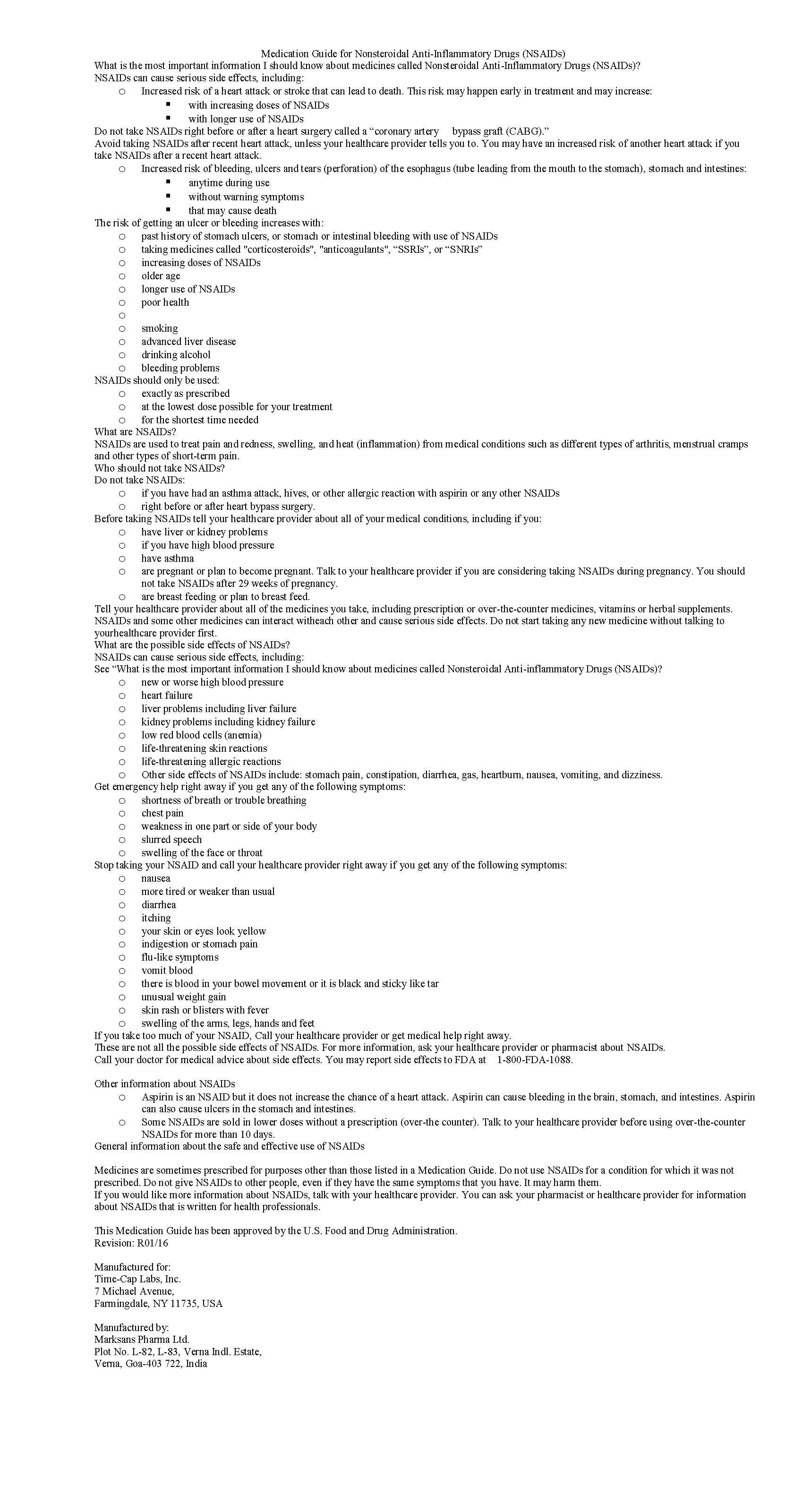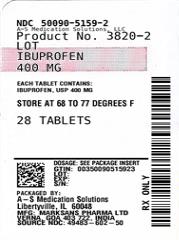 DRUG LABEL: IBUPROFEN
NDC: 50090-5159 | Form: TABLET, FILM COATED
Manufacturer: A-S Medication Solutions
Category: prescription | Type: HUMAN PRESCRIPTION DRUG LABEL
Date: 20210518

ACTIVE INGREDIENTS: IBUPROFEN 400 mg/1 1
INACTIVE INGREDIENTS: SILICON DIOXIDE; CROSCARMELLOSE SODIUM; MAGNESIUM STEARATE; MICROCRYSTALLINE CELLULOSE; POLYETHYLENE GLYCOL, UNSPECIFIED; POLYVINYL ALCOHOL, UNSPECIFIED; STARCH, CORN; TALC; TITANIUM DIOXIDE

IBUPROFEN 400 MG - 600 MG AND 800 MG TABLETS

HOW SUPPLIED

Product: 50090-5159

NDC: 50090-5159-2 28 TABLET, FILM COATED in a BOTTLE

NDC: 50090-5159-0 90 TABLET, FILM COATED in a BOTTLE